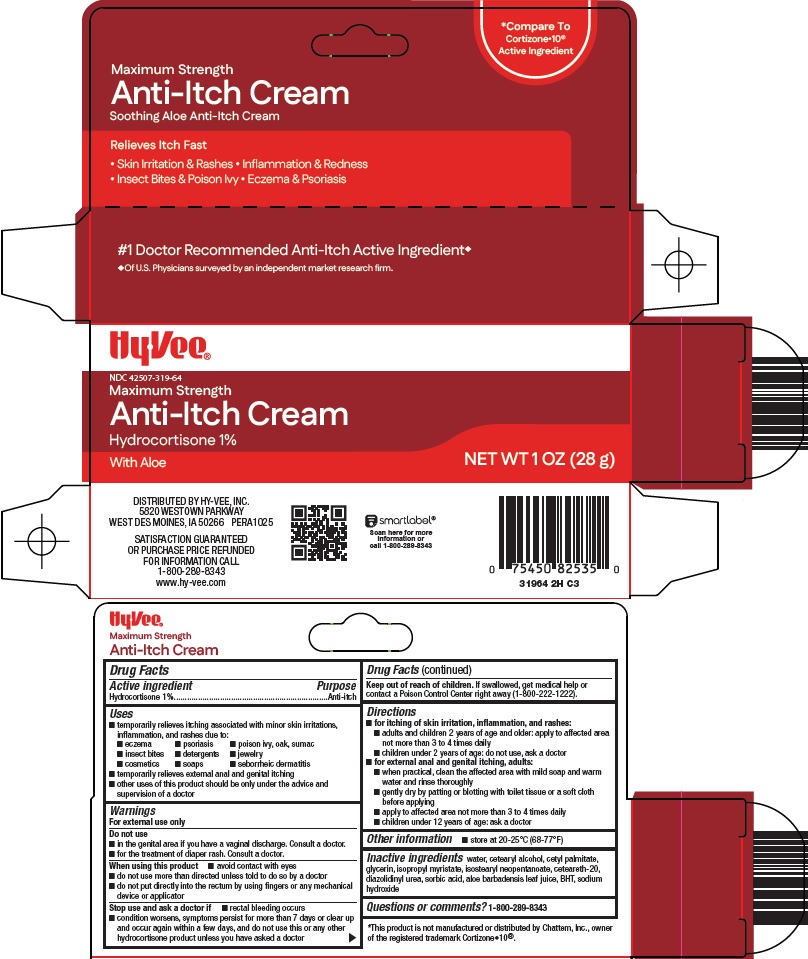 DRUG LABEL: Anti Itch
NDC: 42507-319 | Form: CREAM
Manufacturer: HyVee Inc
Category: otc | Type: HUMAN OTC DRUG LABEL
Date: 20260121

ACTIVE INGREDIENTS: HYDROCORTISONE 1 g/100 g
INACTIVE INGREDIENTS: WATER; CETOSTEARYL ALCOHOL; CETYL PALMITATE; GLYCERIN; ISOPROPYL MYRISTATE; ISOSTEARYL NEOPENTANOATE; POLYOXYL 20 CETOSTEARYL ETHER; DIAZOLIDINYL UREA; SORBIC ACID; ALOE VERA LEAF; BUTYLATED HYDROXYTOLUENE; SODIUM HYDROXIDE

Hy-Vee, Inc. Anti-Itch Cream Drug Facts

Active ingredient

Hydrocortisone 1%

Purpose

Anti-itch

Uses

- temporarily relieves itching associated with minor skin irritations, inflammation, and rashes due to:
  - eczema
  - psoriasis
  - poison ivy, oak, sumac
  - insect bites
  - detergents
  - jewelry
  - cosmetics
  - soaps
  - seborrheic dermatitis
- temporarily relieves external anal and genital itching
- other uses of this product should only be under the advice and supervision of a doctor

Warnings

For external use only

Do not use

- in the genital area if you have a vaginal discharge. Consult a doctor.
- for the treatment of diaper rash. Consult a doctor.

When using this product

- avoid contact with eyes
- do not use more than directed unless told to do so by a doctor
- do not put directly into the rectum by using fingers or any mechanical device or applicator

Stop use and ask a doctor if

- rectal bleeding occurs
- condition worsens, symptoms persist for more than 7 days or clear up and occur again within a few days, and do not use this or any other hydrocortisone product unless you have asked a doctor

Keep out of reach of children.

If swallowed, get medical help or contact a Poison Control Center right away (1-800-222-1222).

Directions

- for itching of skin irritation, inflammation, and rashes:
  - adults and children 2 years of age and older: apply to affected area not more than 3 to 4 times daily
  - children under 2 years of age: do not use, ask a doctor
- for external anal and genital itching, adults:
  - when practical, clean the affected area with mild soap and warm water and rinse thoroughly
  - gently dry by patting or blotting with toilet tissue or a soft cloth before applying
  - apply to affected area not more than 3 to 4 times daily
  - children under 12 years of age: ask a doctor

Other information

- store at 20-25°C (68-77°F)

Inactive ingredients

water, cetearyl alcohol, cetyl palmitate, glycerin, isopropyl myristate, isostearyl neopentanoate, ceteareth-20, diazolidinyl urea, sorbic acid, aloe barbadensis leaf juice, BHT, sodium hydroxide

Questions or comments?

1-800-289-8343

Principal Display Panel

Compare To Cortizone•10® Active Ingredient

Maximum Strength

Anti-Itch Cream

Soothing Aloe Anti-Itch Cream

Relieves Itch Fast

• Skin Irritation & Rashes • Inflammation & Redness • Insect Bites & Poison Ivy • Eczema & Psoriasis

Hy•Vee®

Maximum Strength

Anit-Itch Cream

Hydrocortisone 1%

With Aloe

NET WT 1 OZ (28 g)